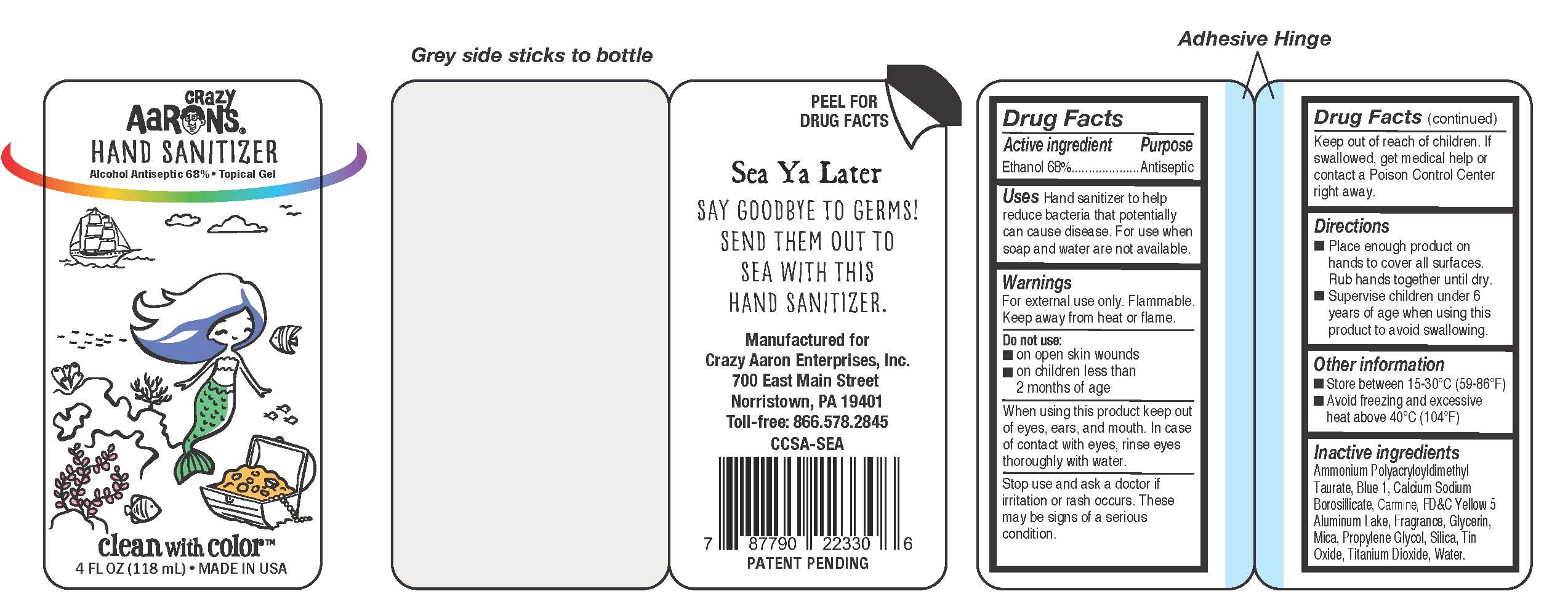 DRUG LABEL: Crazy Aarons Hand Sanitizer 68% Alcohol
NDC: 80032-300 | Form: GEL
Manufacturer: Crazy Aaron Enterprises, Inc.
Category: otc | Type: HUMAN OTC DRUG LABEL
Date: 20200922

ACTIVE INGREDIENTS: ALCOHOL 68 mL/100 mL
INACTIVE INGREDIENTS: FRAGRANCE CLEAN ORC0600327; GLYCERIN; WATER; AMMONIUM POLYACRYLOYLDIMETHYL TAURATE (55000 MPA.S); HYDRATED SILICA; FD&C YELLOW NO. 5; BOROSILICATE GLASS; MICA; DIBUTYLTIN OXIDE; COBALT TITANIUM OXIDE; FD&C BLUE NO. 1; 3-(NONYLOXY)1,2-PROPANEDIOL

Crazy Aarons Sea Ya Later Hand Sanitizer

Drug Facts

Active Ingredient

Ethanol 68% v/v

Purpose

Antiseptic

Use

Hand sanitizer to help reduce bacteria that potentially can cause disease. For use when soap and water are not available.

Warnings

For external use only.

Flammable - Keep away from fire or flame.

When using this product

keep out of eyes, ears, and mouth. In case of contact with eyes, rinse eyes thoroughly with water.

Stop use and ask a doctor if

irritation or rash occurs. These may be signs of a serious condition..

Keep out of reach of children

If swallowed, get medical help or contact a Poison Control Center right away.

DO NOT USE

- on open skin wounds
- on children less than 2 months of age

Directions

• Place enough product on hands to cover all surfaces. Rub hands together briskly until dry.
• Supervise children under 6 years of age when using this product to avoid swallowing

Other information

- Store between 15-30°C (59-86°F)
- Avoid freezing and excessive heat above 40°C (104°F)

Inactive Ingredients

Ammonium Polyacryloyldimethyl Taurate, Blue 1, Calcium Sodium Borosilicate, FD&C Yellow 5 Aluminum Lake, Fragrance, Glycerin, Mica, Propylene Glycol, Silica, Tin Oxide, Titanium Dioxide, Water